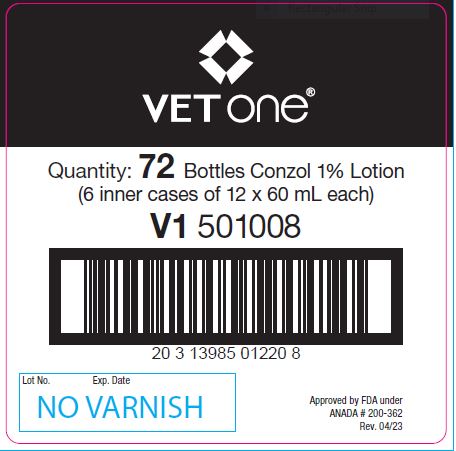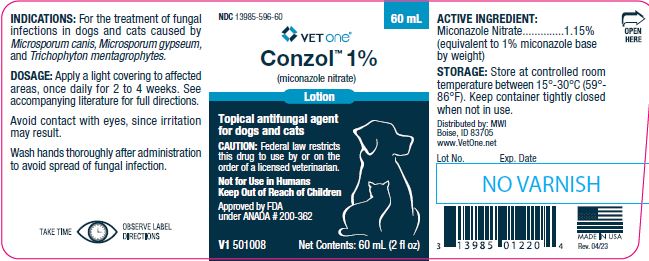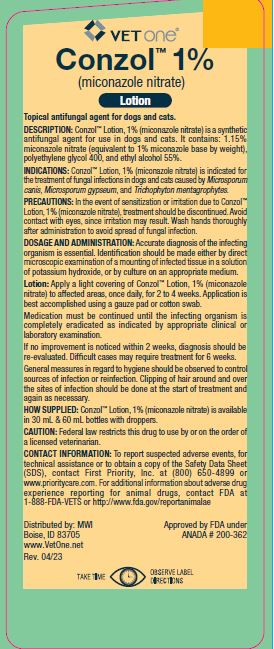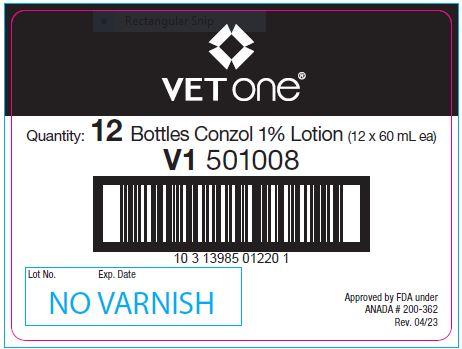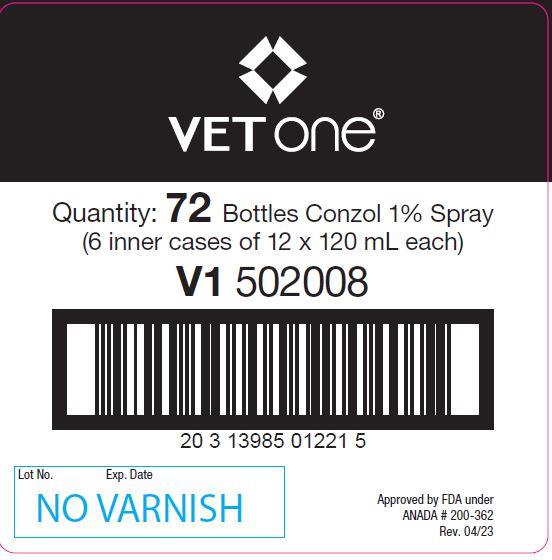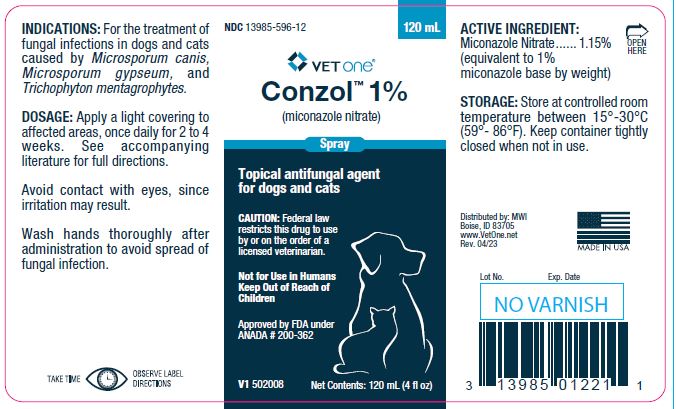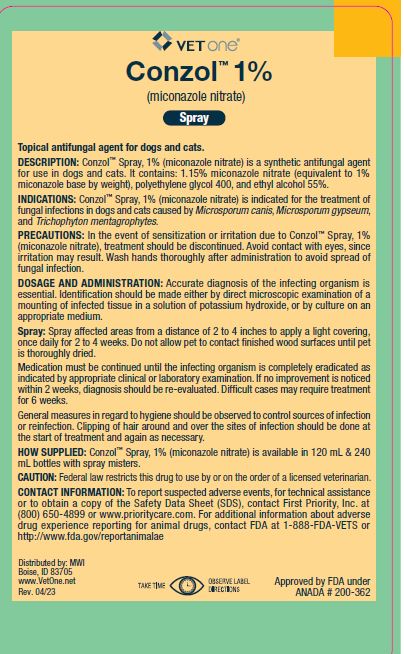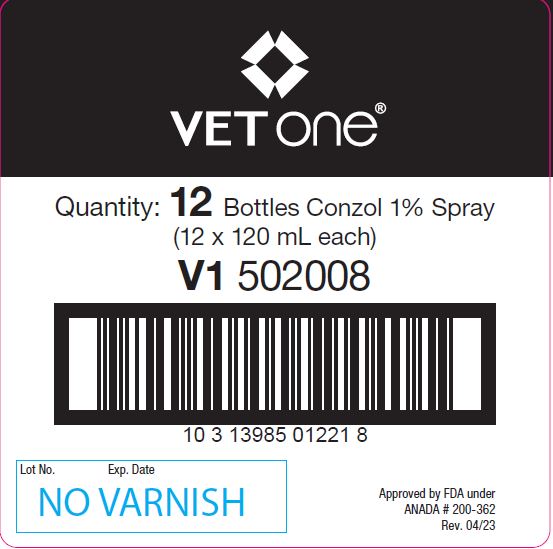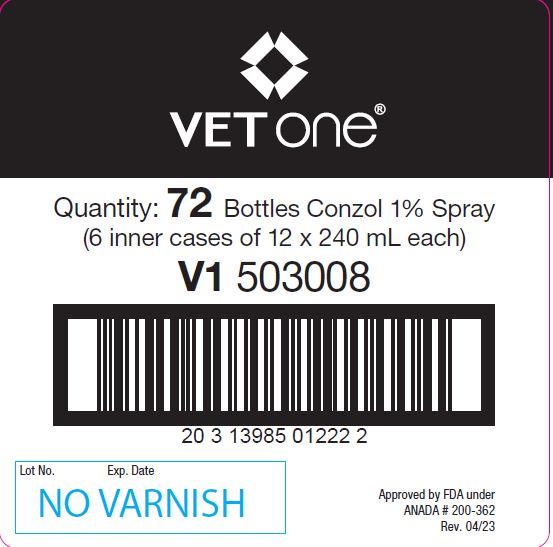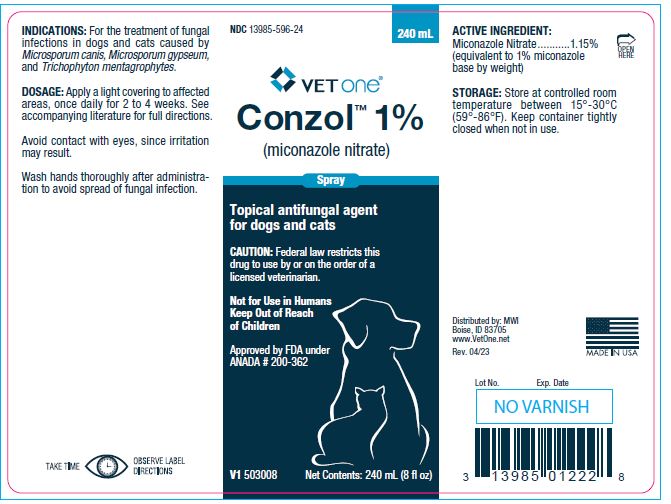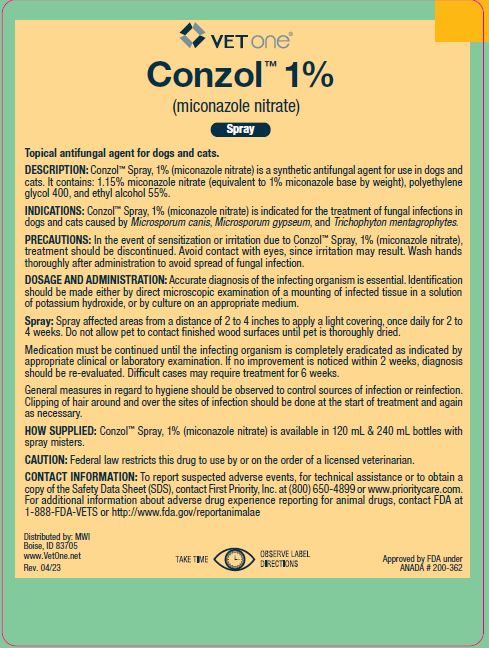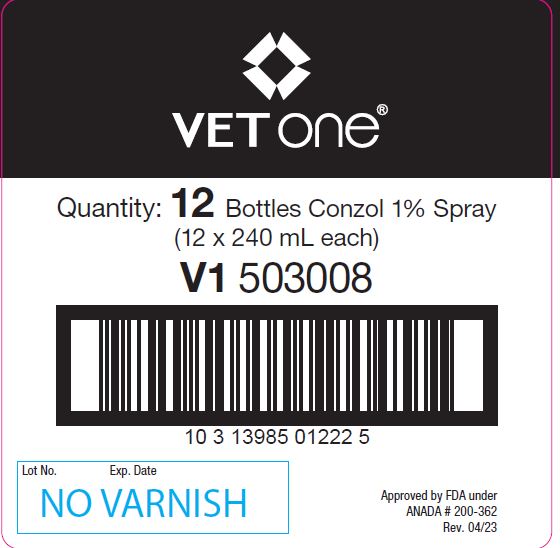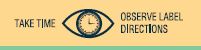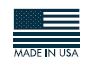 DRUG LABEL: Conzol
NDC: 13985-596 | Form: SPRAY
Manufacturer: MWI
Category: animal | Type: PRESCRIPTION ANIMAL DRUG LABEL
Date: 20260218

ACTIVE INGREDIENTS: MICONAZOLE NITRATE 11.5 mg/1 mL

Conzol™ 1%
(miconazole nitrate)
Lotion & Spray

INFORMATION FOR OWNERS/CAREGIVERS

Topical antifungal agent for dogs and cats.

PRECAUTIONS

CAUTION: Federal law restricts this drug to use by or on the order of a licensed veterinarian.

Not for Use in Humans
Keep Out of Reach of Children

Approved by FDA under ANADA # 200-362

DESCRIPTION:

Conzol™ Lotion, 1% (miconazole nitrate) & Conzol™ Spray, 1% (miconazole nitrate) is a synthetic antifungal agent for use in dogs and cats. It contains: 1.15% miconzole nitrate (equivalent to 1% miconzole base by weight), polyethylene glycol 400, ethyl alcohol 55%.

INDICATIONS:

Conzol™ Lotion, 1% (miconzole nitrate) & Conzol™ Spray, 1% (miconzole nitrate) is indicated for the treatment of fungal infections in dogs and cats caused by Microsporum canis, Microsporum gypseum, and Trichophyton mentagrophytes.

PRECAUTIONS:

In the event of sensitization or irritation due to Conzol™ Lotion, 1% (miconazole nitrate) & Conzol™ Spray, 1% (miconazole nitrate), treatment should be discontinued. Avoid contact with eyes, since irritation may result. Wash hands thoroughly after administration to avoid spread of fungal infection.

DOSAGE AND ADMINISTRATION:

Accurate diagnosis of the infecting organism is essential. Identification should be made either by direct microscopic examination of a mounting of infected tissue in a solution of potassium hydroxide, or by culture on an appropriate medium.

Lotion: Apply a light covering of Conzol™ Lotion, 1% (miconazole nitrate) to affected areas, once daily, for 2 to 4 weeks. Application is best accomplished using a gauze pad or cotton swab.

Spray: Spray affected areas from a distance of 2 to 4 inches to apply a light covering, once daily for 2 to 4 weeks. Do not allow pet to contact finished wood surfaces until pet is thoroughly dried.

Medication must be continued until the infecting organism is completely eradicated as indicated by appropriate clinical or laboratory examination. If no improvement is noticed within 2 weeks, diagnosis should be re-evaluated. Difficult cases may require treatment for 6 weeks.

General measures in regard to hygiene should be observed to control sources of infection or reinfection. Clipping of hair around and over the sites of infection should be done at the start of treatment and again as necessary.

ACTIVE INGREDIENT:
Miconazole Nitrate...........1.15%
(equivalent to 1% miconazole base by weight)

STORAGE:

Store at controlled room temperature between 15°-30°C (59°-86°F). Keep container tightly closed when not in use.

HOW SUPPLIED:

Lotion:

Conzol™ Lotion, 1% (miconazole nitrate) is available in 30 and 60 mL bottles with droppers.

Spray:

Conzol™ Spray, 1% (miconazole nitrate) is available in 120 mL & 240 mL bottles with spray misters.

CAUTION:

Federal law restricts this drug to use by or on the order of a licensed veterinarian.

CONTACT INFORMATION:

To report suspected adverse events, for technical assistance or to obtain a copy of the Safety Data Sheet (SDS), contact First Priority, Inc. at (800) 650-4899 or www.prioritycare.com. For additional information about adverse drug experience reporting for animal drugs, contact FDA at 1-888-FDA-VETS or http://www.fda.gov/reportanimalae

INFORMATION FOR OWNERS/CAREGIVERS

Distributed by: MWI
Boise, ID 83705
www.VetOne.net
Rev. 04/23

Approved by FDA under ANADA # 200-362